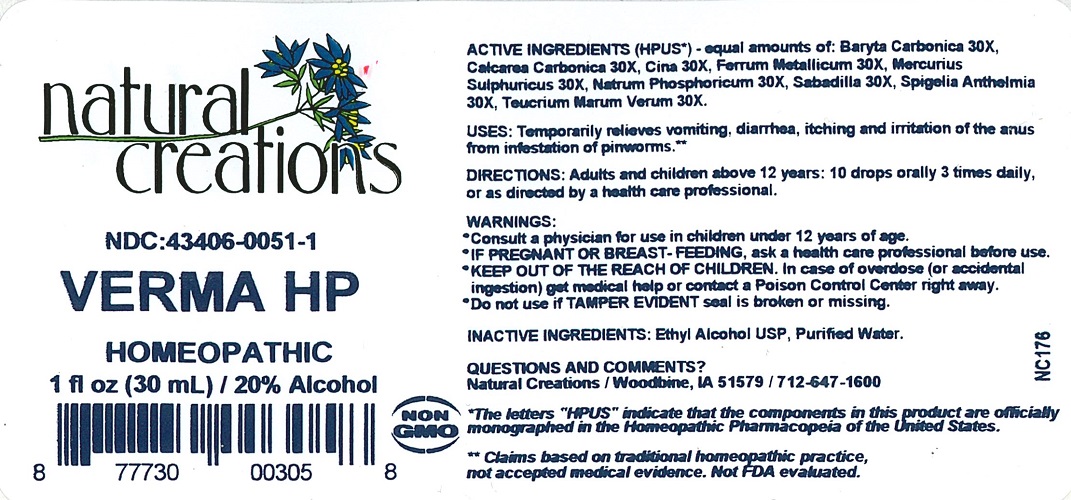 DRUG LABEL: VERMA HP
NDC: 43406-0051 | Form: LIQUID
Manufacturer: Natural Creations, Inc.
Category: homeopathic | Type: HUMAN OTC DRUG LABEL
Date: 20200526

ACTIVE INGREDIENTS: BARIUM CARBONATE 30 [hp_X]/1 mL; OYSTER SHELL CALCIUM CARBONATE, CRUDE 30 [hp_X]/1 mL; ARTEMISIA CINA FLOWER 30 [hp_X]/1 mL; IRON 30 [hp_X]/1 mL; MERCURIC SULFATE 30 [hp_X]/1 mL; SODIUM PHOSPHATE, DIBASIC, HEPTAHYDRATE 30 [hp_X]/1 mL; SCHOENOCAULON OFFICINALE SEED 30 [hp_X]/1 mL; SPIGELIA ANTHELMIA 30 [hp_X]/1 mL; TEUCRIUM MARUM 30 [hp_X]/1 mL
INACTIVE INGREDIENTS: WATER; ALCOHOL

VERMA HP

ACTIVE INGREDIENT

ACTIVE INGREDIENTS (HPUS*) equal amounts of: Baryta Carbonica 30X, Calcarea Carbonica 30X, Cina 30X, Ferrum Metallicum 30X, Mercurius Sulphuricus 30X, Natrum Phosphoricum 30X, Sabadilla 30X, Spigelia Anthelmia 30X, Teucrium Marum Verum 30X

KEEP OUT OF REACH OF CHILDREN

KEEP OUT OF THE REACH OF CHILDREN. In case of overdose (or accidental ingestion) get medical help or contact a Poison Control Center right away.

INDICATIONS AND USAGE

USES: Temporarily relieves vomiting, diarrhea, itching and irritation of the anus from infestation of pinworms.**

WARNING:

- Consult a physician for use in children under 12 years of age.
- IF PREGNANT OR BREAST-FEEDING, ask a health care professional before use.
- KEEP OUT OF THE REACH OF CHILDREN. In case of overdose (or accidental ingestion) get medical help or contact a Poison Control Center right away.
- Do not use if TAMPER EVIDENT seal is broken or missing.

DOSAGE AND ADMINISTRATION

DIRECTIONS: Adults and children above 12 years: 10 drops orally 3 times daily, or as directed by a health care professional.

INACTIVE INGREDIENTS: Ethyl Alcohol USP, Purified Water.

QUESTIONS AND COMMENTS?
Natural Creations, Inc. / Woodbine, IA 51579 / 712-647-1600

PURPOSE

USES: Temporarily relieves vomiting, diarrhea, itching & irritation of the anus from infestation of pinworms.**

PACKAGE LABEL

NDC: 43406-0051-1

VERMA HP

HOMEOPATHIC

1 fl oz (30 mL) / 20% Alcohol

UPC: 877730003058